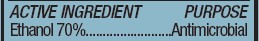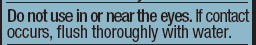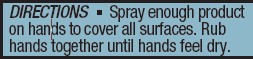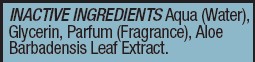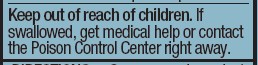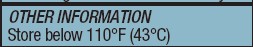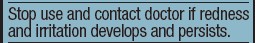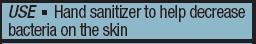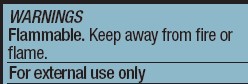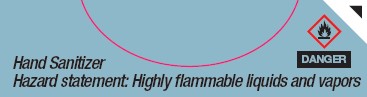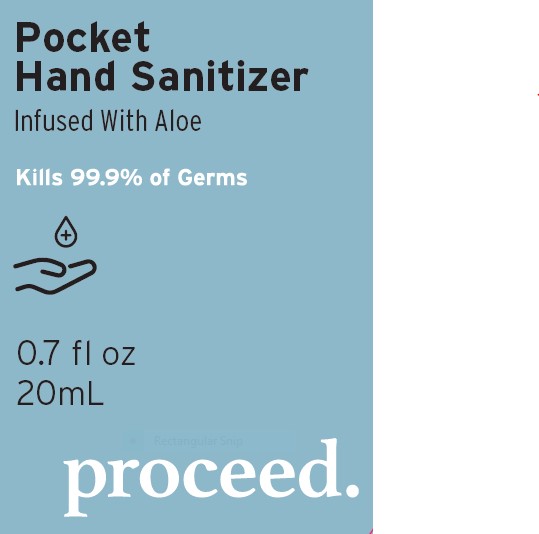 DRUG LABEL: Hand Sanitizer
NDC: 80380-070 | Form: SPRAY
Manufacturer: Shedrain Corporation
Category: otc | Type: HUMAN OTC DRUG LABEL
Date: 20201023

ACTIVE INGREDIENTS: ALCOHOL 70 mL/100 mL
INACTIVE INGREDIENTS: GLYCERIN 3 mL/100 mL; ALOE VERA LEAF 0.1 mL/100 mL; WATER

Active Ingredient(s)

Ethanol 70%. Purpose: Antimicrobial

Purpose

Hand sanitizer to help decrease bacteria on the skin.

Use

Spray enough product on hands to cover all surfaces. Rub hands together until hands feel dry.

Warnings

Flammable. Keep away from fire or flame For external use only.Highly falmmable liquids and vapors.

Do not use in or near the eyes. If contact occurs, flush thoroughly with water.

Stop use and contact doctor if redness and irritation develops and persists.

Keep out of reach of children. If swallowed, get medical help or contact the Poison Control Center right away.

Other information

Store below 110°F (43°C)

Inactive ingredients

Aqua (Water), Glycerin, Parfum (Fragrance), Aloe Barbadensis Leaf Extract.

DOSAGE AND ADMINISTRATION

Spray enough product on hands to cover all surfaces. Rub hands together until hands feel dry.

Package Label - Principal Display Panel

Pocket hand sanitizer